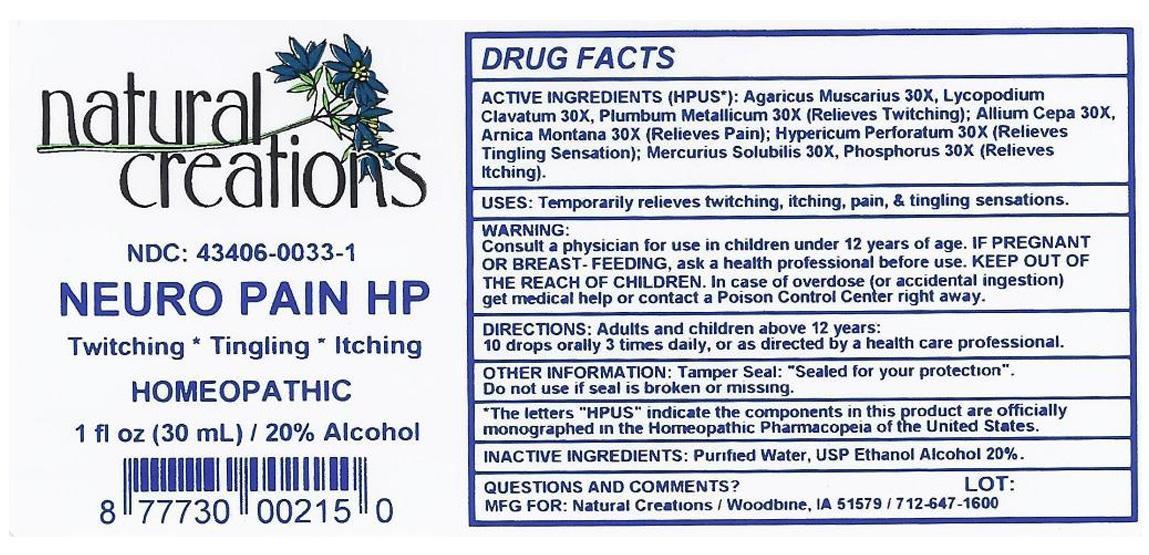 DRUG LABEL: NEURO PAIN HP
NDC: 43406-0033 | Form: LIQUID
Manufacturer: Natural Creations, Inc.
Category: homeopathic | Type: HUMAN OTC DRUG LABEL
Date: 20121108

ACTIVE INGREDIENTS: AMANITA MUSCARIA VAR. MUSCARIA 30 [hp_X]/1 mL; LYCOPODIUM CLAVATUM SPORE 30 [hp_X]/1 mL; MERCURIUS SOLUBILIS 30 [hp_X]/1 mL; PHOSPHORUS 30 [hp_X]/1 mL; LEAD 30 [hp_X]/1 mL; ONION 30 [hp_X]/1 mL; ARNICA MONTANA ROOT 30 [hp_X]/1 mL; HYPERICUM PERFORATUM 30 [hp_X]/1 mL
INACTIVE INGREDIENTS: WATER; ALCOHOL

NEURO PAIN HP

ACTIVE INGREDIENT

ACTIVE INGREDIENTS (HPUS*): Agaricus Muscarius 30X, Allium Cepa 30X, Arnica Montana 30X, Hypericum Perforatum 30X, Lycopodium Clavatum 30X, Mercurius Solubilis 30X, Phosphorus 30X, Plumbum Metallicum 30X

INDICATIONS AND USAGE

USES: Temporarily relieves twitching, itching, pain & tingling sensations.

WARNING:

Consult a physician for use in children under 12 years of age. IF PREGNANT OR BREAST-FEEDING, ask a health care professinal before use. KEEP OUT OF THE REACH OF CHILDREN. In case of overdose (or accidental ingestion) get medical help or contact a Poison Control Center right away.

DOSAGE AND ADMINISTRATION

DIRECTIONS: Adults and children above 12 years: 10 drops orally 3 times daily, or as directed by a health care professional.

OTHER INFORMATION: Tamper Seal: "Sealed for your protection."

Do not use if seal is broken or missing.

REFERENCES

*The letters "HPUS" indicate the components in the product are officially monographed in the Homeopathic Pharmacopeia of the United States.

INACTIVE INGREDIENTS: Purified Water, USP Ethanol Alcohol 20%

QUESTIONS AND COMMENTS?

MFG FOR: Natural Creations / Woodbine, IA / 51579 712.647.1600

LOT:

PURPOSE

UES: Temporarily relieves twitching, itching, pain & tingling sensations.

KEEP OUT OF REACH OF CHILDREN

KEEP OUT OF THE REACH OF CHILDREN. In case of overdose (or accidental ingestion) get medical help or contact a Poison Control Center.

PACKAGE LABEL

NDC: 43406-0033-1

NEURO PAIN HP

Twtiching * Tingling * Itching

HOMEOPATHIC

1 fl oz (30 mL) / 20% Alcohol

UPC: 877730002150